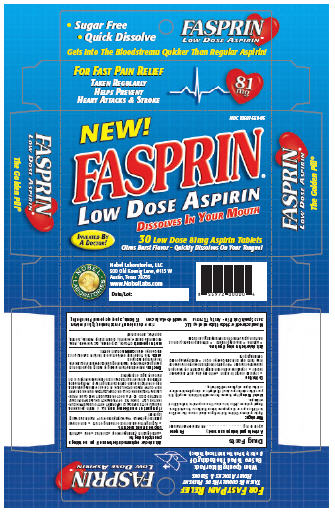 DRUG LABEL: Fasprin
NDC: 10597-559 | Form: TABLET, ORALLY DISINTEGRATING
Manufacturer: Nobel Laboratories, LLC
Category: otc | Type: HUMAN OTC DRUG LABEL
Date: 20101130

ACTIVE INGREDIENTS: ASPIRIN 81 mg/1 1
INACTIVE INGREDIENTS: CITRIC ACID MONOHYDRATE; CROSPOVIDONE; D&C YELLOW NO. 10; GLUCOSAMINE; MANNITOL; SODIUM STEARYL FUMARATE; SORBITOL; ZINC GLUCONATE

Drug Facts

Active Ingredient (In Each Tablet)

Aspirin 81 mg

Purpose

Pain Reliever/Fever Reducer

Uses

For temporary relief of minor aches and pains

Warnings:

Reye's syndrome: Children and teenagers should not use this medicine
for chicken pox or flu symptoms before a doctor is consulted about
Reye's syndrome, a rare but serious illness reported to be associated
with aspirin.
Alcohol Warning: If you consume 3 or more alcoholic drinks every day, ask
your doctor whether you should take aspirin or other pain relievers/fever
reducers. Aspirin may cause stomach bleeding.

DO NOT USE

- If you are allergic to aspirin

- With any other pain reliever/fever reducer

- If you have ever had an allergic reaction to any other pain reliever/fever reducer

- For pain for more than 10 days or for fever for more than 3 days unless directed by a doctor

- With any other product containing aspirin

Ask doctor before using if you have:

- Asthma
- Bleeding problems
- Stomach problems (such as heartburn, upset stomach or stomach pain) gastric ulcers

Ask a doctor or pharmacist before use if you are taking a prescription drug for:

- Anticoagulation (thinning of blood)
- Diabetes
- Gout
- Arthritis

Stop use and ask a doctor if:

- Ringing in the ears or loss of hearing occurs
- Pain or fever persists or gets worse
- New symptoms occur
- Redness or swelling is present

If pregnant or breast-feeding baby,

ask a health professional before use. IT IS ESPECIALLY IMPORTANT NOT TO USE ASPIRIN DURING THE LAST 3 MONTHS OF PREGNANCY UNLESS SPECIFICALLY DIRECTED TO DO SO BY A DOCTOR BECAUSE IT MAY CAUSE PROBLEMS IN THE UNBORN CHILD OR COMPLICATIONS DURING DELIVERY.

KEEP OUT OF REACH OF CHILDREN. In case of overdose, get medical help or contact a Poison Control Center right away. Prompt medical attention is critical for adults as well as for children even if you do not notice any signs or symptoms.

Directions

Directions: Remove tablet from backing by bending at perforation and
peeling back cover. Place tablet on tongue and allow saliva to dissolve the
tablet for rapid absorption.
Adults: Take 1 tablet daily, do not exceed 36 tablets in 24 hours, or as
directed by a doctor. Children: Consult a doctor.

Inactive Ingredients:

Citric Acid, Crospovidone, D and C Yellow #10, Flavor, Glucosamine Sulfate-K, Mannitol, Sodium Stearyl Fumarate, Sorbitol, Sunnette K, Zinc Gluconate

Manufactured for: Nobel Laboratories, LLC

3413 Spanish Oak Drive Austin, TX 787314
www.NobelLabs.com

STORAGE AND HANDLING

Store Product Below 90 degrees F. Protect from heat, light and moisture.

U.S Patents 6,596,708 / 6,930,099 and Patents Pending